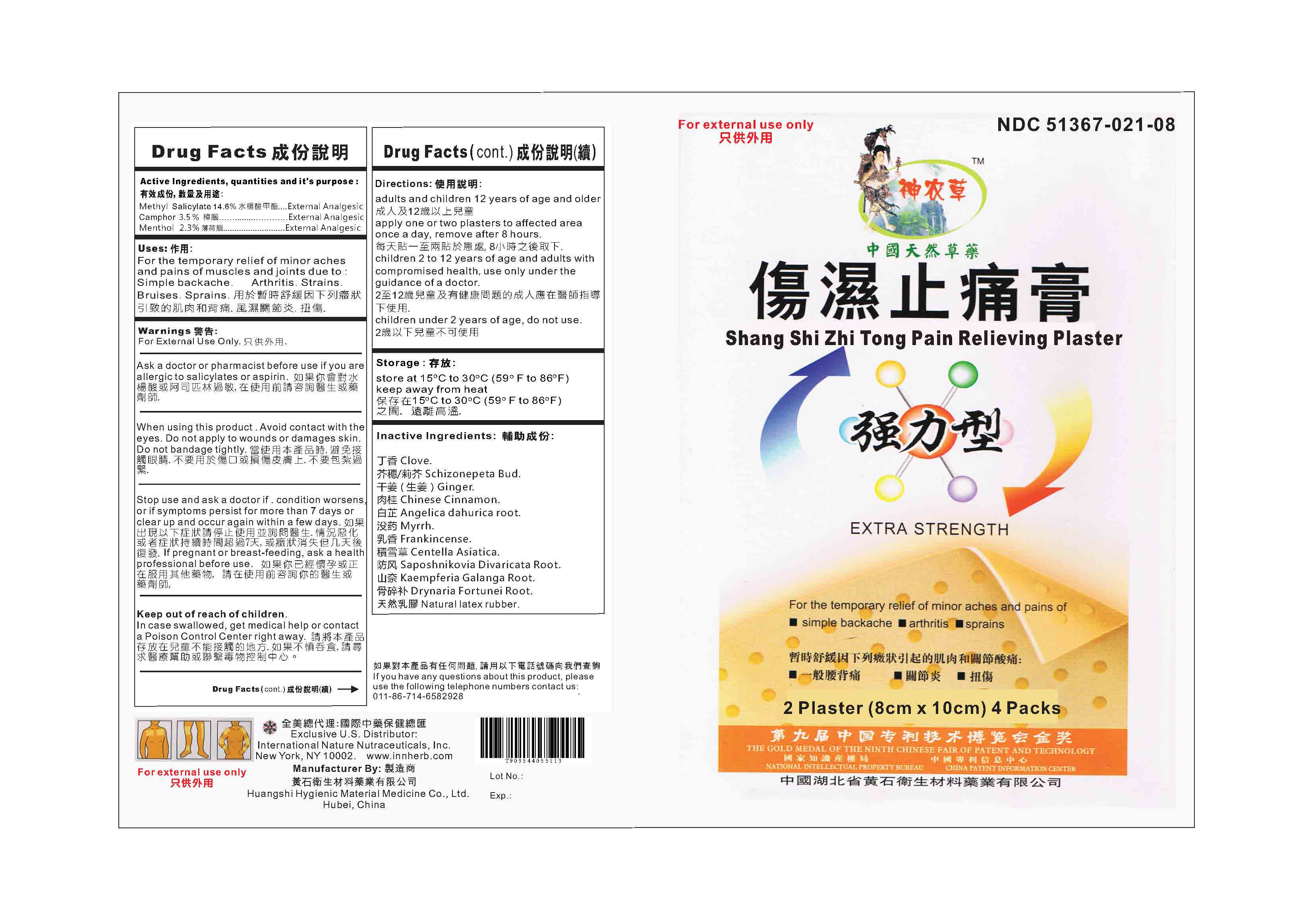 DRUG LABEL: Shang Shi Zhi Tong Pain Relieving Plaster
NDC: 51367-021 | Form: PLASTER
Manufacturer: International Nature Nutraceuticals
Category: otc | Type: HUMAN OTC DRUG LABEL
Date: 20241219

ACTIVE INGREDIENTS: METHYL SALICYLATE 120.8 mg/1 1; CAMPHOR (NATURAL) 116 mg/1 1; MENTHOL 116 mg/1 1
INACTIVE INGREDIENTS: CLOVE; NEPETA TENUIFOLIA FLOWERING TOP; GINGER; CHINESE CINNAMON; ANGELICA DAHURICA ROOT; MYRRH; FRANKINCENSE; CENTELLA ASIATICA; SAPOSHNIKOVIA DIVARICATA ROOT; KAEMPFERIA GALANGA ROOT; DRYNARIA FORTUNEI ROOT; NATURAL LATEX RUBBER

Drug Listing

Active Ingredients:

Methyl Salicylate: 14.6%...External Analgesic

Camphor: 3.5%....External Analgesic

Menthol: 2.3%....Extermal Analgesic

Uses:

For the temporary relief of minor aches and pains of muscles and joints due to: simple backache, arthritis, strains, bruises, strains

Warnings:

For external use only

When Using this product:

Avoid contact with the eyes. Do not apply to wounds or damaged skin. Do not bandage tightly.

Ask a doctor or pharmacist before use if:

You are allergic to salicylates or asprin.

Stop use and ask a doctor if:

Condition worsens, or if symptoms persist for more than 7 days, or clear up and occur again within a few days.

If pregnant or breast-feeding, ask a health professional before use.

Keep out of reach of children

In case swallowed, get medical help or contact a poison control center right away.

Directions:

Adults and children 12 years of age and older: apply one or two plasters to affected area once a day, remove after 8 hours.

Children 2 to 12 years of age and adults with compromised health: use only under the guidance of a doctor

Children under 2 years of age: do not use.

Storage

Store at 15°C to 30°C (59°F to 86°F)

Keep away from heat

Inactive Ingredients

Clove, schizonpeta bud, Chinese cinnamon, angelica dahurica root, myrrh, frankincense, centella asiatica, saposhnikovia divaricata root, kaemferia galanga root, ginger,drynaria fortunei root, natural latex rubber